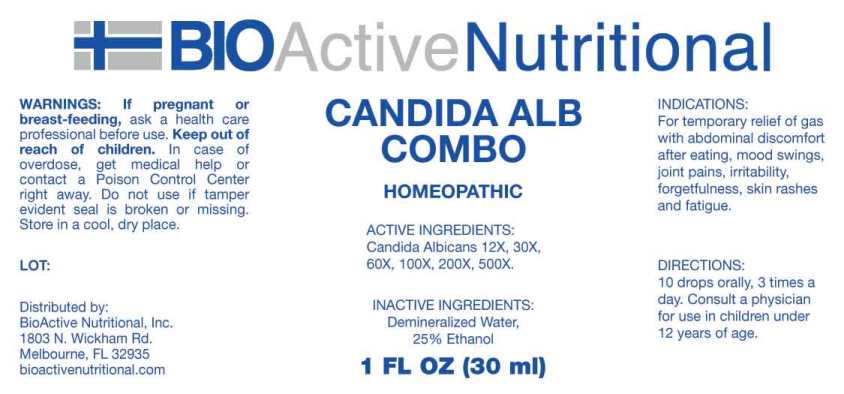 DRUG LABEL: Candida Alb Combo
NDC: 43857-0573 | Form: LIQUID
Manufacturer: BioActive Nutritional, Inc.
Category: homeopathic | Type: HUMAN OTC DRUG LABEL
Date: 20230607

ACTIVE INGREDIENTS: CANDIDA ALBICANS 12 [hp_X]/1 mL
INACTIVE INGREDIENTS: WATER; ALCOHOL

Drug Facts:

ACTIVE INGREDIENTS:

Candida Albicans 12X, 30X, 60X, 100X, 200X, 500X.

INDICATIONS:

For temporary relief of gas with abdominal discomfort after eating, mood swings, joint pains, irritability, forgetfulness, skin rashes and fatigue.

WARNINGS:

If pregnant or breast-feeding, ask a health care professional before use.

Keep out of reach of children. In case of overdose, get medical help or contact a Poison Control Center right away.

Do not use if tamper evident seal is broken or missing.

Store in cool, dry place.

DIRECTIONS:

10 drops orally, 3 times a day. Consult a physician for use in children under 12 years of age.

INACTIVE INGREDIENTS:

Demineralized Water, 25% Ethanol

Keep out of reach of children. In case of overdose, get medical help or contact a Poison Control Center right away.

INDICATIONS:

For temporary relief of gas with abdominal discomfort after eating, mood swings, joint pains, irritability, forgetfulness, skin rashes and fatigue.

QUESTIONS:

Distributed by:
BioActive Nutritional, Inc.
1803 N. Wickham Rd.
Melbourne, FL 32935
bioactivenutritional.com

PACKAGE LABEL DISPLAY:

BIOActive Nutritional

CANDIDA ALB COMBO

HOMEOPATHIC

1 FL OZ (30ml)